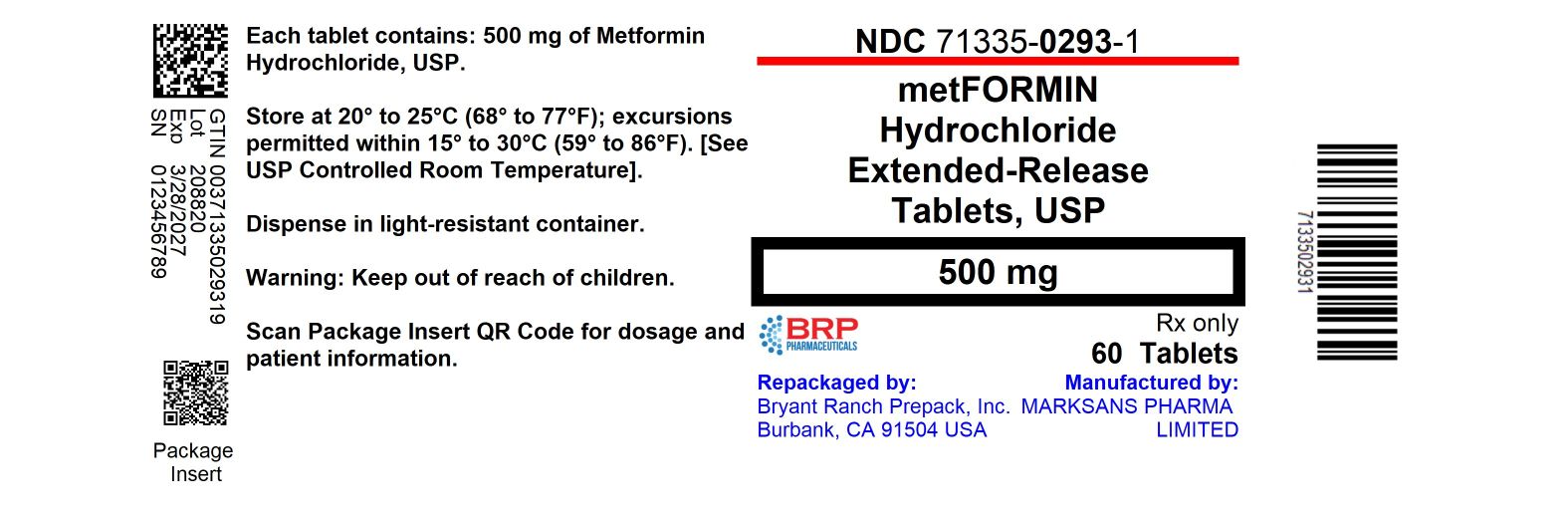 DRUG LABEL: METFORMIN HYDROCHLORIDE EXTENDED RELEASE
NDC: 71335-0293 | Form: TABLET, EXTENDED RELEASE
Manufacturer: Bryant Ranch Prepack
Category: prescription | Type: HUMAN PRESCRIPTION DRUG LABEL
Date: 20250328

ACTIVE INGREDIENTS: METFORMIN HYDROCHLORIDE 500 mg/1 1
INACTIVE INGREDIENTS: HYPROMELLOSE 2208 (100 MPA.S); SILICON DIOXIDE; MAGNESIUM STEARATE

METFORMIN ER TABLETS

INDICATIONS AND USAGE

Metformin Hydrochloride Extended-Release Tablets, USP is indicated as an adjunct to diet and exercise to improve glycemic control in adults with type 2 diabetes mellitus.

HOW SUPPLIED

Metformin Hydrochloride Extended-Release Tablets, USP 500 mg arewhite to off-white, capsule shaped, biconvex tablets, debossed with '101' on one side and plain on other side.

NDC: 71335-0293-1: 60 Tablets in a BOTTLE

NDC: 71335-0293-2: 30 Tablets in a BOTTLE

NDC: 71335-0293-3: 100 Tablets in a BOTTLE

NDC: 71335-0293-4: 90 Tablets in a BOTTLE

NDC: 71335-0293-5: 120 Tablets in a BOTTLE

NDC: 71335-0293-6: 15 Tablets in a BOTTLE

NDC: 71335-0293-7: 45 Tablets in a BOTTLE

NDC: 71335-0293-8: 180 Tablets in a BOTTLE

NDC: 71335-0293-9: 20 Tablets in a BOTTLE

Storage

Store at 20°–25° C (68°–77° F); excursions permitted to 15°–30° C (59°–86° F). [See USP Controlled Room Temperature.]

Dispense in a light-resistant container.

Repackaged/Relabeled by:
Bryant Ranch Prepack, Inc.
Burbank, CA 91504

DOSAGE AND ADMINISTRATION

There is no fixed dosage regimen for the management of hyperglycemia in patients with type 2 diabetes with metformin hydrochloride extended-release tablets or any other pharmacologic agent. Dosage of metformin hydrochloride extended-release tablets must be individualized on the basis of both effectiveness and tolerance, while not exceeding the maximum recommended daily doses. The maximum recommended daily dose of metformin hydrochloride extended-release tablets in adults is 2000 mg.
Metformin hydrochloride extended-release tablets should generally be given once daily with the evening meal. Metformin hydrochloride extended-release tablets should be started at a low dose, with gradual dose escalation, both to reduce gastrointestinal side effects and to permit identification of the minimum dose required for adequate glycemic control of the patient.
During treatment initiation and dose titration (see Recommended Dosing Schedule), fasting plasma glucose should be used to determine the therapeutic response to metformin hydrochloride extended-release tablets and identify the minimum effective dose for the patient. Thereafter, glycosylated hemoglobin should be measured at intervals of approximately three months. The therapeutic goal should be to decrease both fasting plasma glucose and glycosylated hemoglobin levels to normal or near normal by using the lowest effective dose of metformin hydrochloride extended-release tablets, either when used as monotherapy or in combination with sulfonylurea or insulin.
Monitoring of blood glucose and glycosylated hemoglobin will also permit detection of primary failure, i.e., inadequate lowering of blood glucose at the maximum recommended dose of medication, and secondary failure, i.e., loss of an adequate blood glucose lowering response after an initial period of effectiveness.
Short-term administration of metformin hydrochloride extended-release tablets may be sufficient during periods of transient loss of control in patients usually well-controlled on diet alone.
Metformin hydrochloride extended-release tablets must be swallowed whole and never crushed or chewed. Occasionally, the inactive ingredients of metformin hydrochloride extended-release tablets will be eliminated in the feces as a soft, hydrated mass. (See Patient information printed below.)
Recommended Dosing Schedule
Adults - In general, clinically significant responses are not seen at doses below 1500 mg per day. However, a lower recommended starting dose and gradually increased dosage is advised to minimize gastrointestinal symptoms.
The usual starting dose of metformin hydrochloride extended-release tablet is 500 mg once daily with the evening meal. Dosage increases should be made in increments of 500 mg weekly, up to a maximum of 2000 mg once daily with the evening meal. If glycemic control is not achieved on metformin hydrochloride extended-release tablets 2000 mg once daily, a trial of metformin hydrochloride extended-release tablets 1000 mg twice daily should be considered.
In a randomized trial, patients currently treated with metformin hydrochloride tablets were switched to metformin hydrochloride extended-release tablets. Results of this trial suggest that patients receiving metformin hydrochloride tablets treatment may be safely switched to metformin hydrochloride extended-release tablets once daily at the same total daily dose, up to 2000 mg once daily. Following a switch from metformin hydrochloride tablets to metformin hydrochloride extended-release tablets, glycemic control should be closely monitored and dosage adjustments made accordingly
Pediatrics – Safety and effectiveness of metformin hydrochloride extended-release tablets in pediatric patients have not been established.
Transfer From Other Antidiabetic Therapy
When transferring patients from standard oral hypoglycemic agents other than chlorpropamide to metformin hydrochloride extended-release tablets, no transition period generally is necessary. When transferring patients from chlorpropamide, care should be exercised during the first two weeks because of the prolonged retention of chlorpropamide in the body, leading to overlapping drug effects and possible hypoglycemia.
Concomitant Metformin Hydrochloride Extended-Release Tablets and Oral Sulfonylurea
Therapy in Adult Patients
If patients have not responded to four weeks of the maximum dose of metformin hydrochloride extended-release tablets monotherapy, consideration should be given to gradual addition of an oral sulfonylurea while continuing metformin hydrochloride extended-release tablets at the maximum dose, even if prior primary or secondary failure to a sulfonylurea has occurred. Clinical and pharmacokinetic drug-drug interaction data are currently available only for metformin plus glyburide (glibenclamide).
With concomitant metformin hydrochloride extended-release tablets and sulfonylurea therapy, the desired control of blood glucose may be obtained by adjusting the dose of each drug. However, attempts should be made to identify the minimum effective dose of each drug to achieve this goal. With concomitant metformin hydrochloride extended-release tablets and sulfonylurea therapy, the risk of hypoglycemia associated with sulfonylurea therapy continues and may be increased. Appropriate precautions should be taken. (See Package Insert of the respective sulfonylurea.)
If patients have not satisfactorily responded to one to three months of concomitant therapy with the maximum dose of metformin hydrochloride extended-release tablets and the maximum dose of an oral sulfonylurea, consider therapeutic alternatives including switching to insulin with or without metformin hydrochloride extended-release tablets.
Concomitant Metformin Hydrochloride Extended-Release Tablets and Insulin Therapy in Adult Patients

The current insulin dose should be continued upon initiation of metformin hydrochloride extended-release tablets therapy. Metformin hydrochloride extended-release tablets therapy should be initiated at 500 mg once daily in patients on insulin therapy. For patients not responding adequately, the dose of metformin hydrochloride extended-release tablets should be increased by 500 mg after approximately 1 week and by 500 mg every week thereafter until adequate glycemic control is achieved. The maximum recommended daily dose is 2000 mg for metformin hydrochloride extended-release tablets. It is recommended that the insulin dose be decreased by 10% to 25% when fasting plasma glucose concentrations decrease to less than 120 mg/dL in patients receiving concomitant insulin and metformin hydrochloride extended-release tablets. Further adjustment should be individualized based on glucose-lowering response.

Specific Patient Populations
Metformin hydrochloride extended-release tablets are not recommended for use in pregnancy. Metformin hydrochloride extended-release tablet is not recommended in pediatric patients (below the age of 17 years).
The initial and maintenance dosing of metformin hydrochloride extended-release tablets should be conservative in patients with advanced age, due to the potential for decreased renal function in this population. Any dosage adjustment should be based on a careful assessment of renal function. Generally, elderly, debilitated, and malnourished patients should not be titrated to the maximum dose of metformin hydrochloride extended-release tablets.
Monitoring of renal function is necessary to aid in prevention of lactic acidosis, particularly in the elderly.

WARNINGS

WARNING: LACTIC ACIDOSIS

Postmarketing cases of metformin-associated lactic acidosis have resulted in death, hypothermia, hypotension, and resistant bradyarrhythmias. The onset of metformin associated lactic acidosis is often subtle, accompanied only by nonspecific symptoms such as malaise, myalgias, respiratory distress, somnolence, and abdominal pain. Metforminassociated lactic acidosis was characterized by elevated blood lactate levels (>5 mmol/Liter), anion gap acidosis (without evidence of ketonuria or ketonemia), an increased lactate/pyruvate ratio; and metformin plasma levels generally >5 mcg/mL (see PRECAUTIONS).

Risk factors for metformin-associated lactic acidosis include renal impairment, concomitant use of certain drugs (e.g. carbonic anhydrase inhibitors such as topiramate), age 65 years old or greater, having a radiological study with contrast, surgery and other procedures, hypoxic states (e.g., acute congestive heart failure), excessive alcohol intake, and hepatic impairment.

Steps to reduce the risk of and manage metformin-associated lactic acidosis in these high risk groups are provided (see DOSAGE AND ADMINISTRATION, CONTRAINDICATIONS, and PRECAUTIONS).

If metformin-associated lactic acidosis is suspected, immediately discontinue metformin and institute general supportive measures in a hospital setting. Prompt hemodialysis is recommended (see PRECAUTIONS).

PACKAGE LABEL

Metformin Hcl ER 500mg Tablet